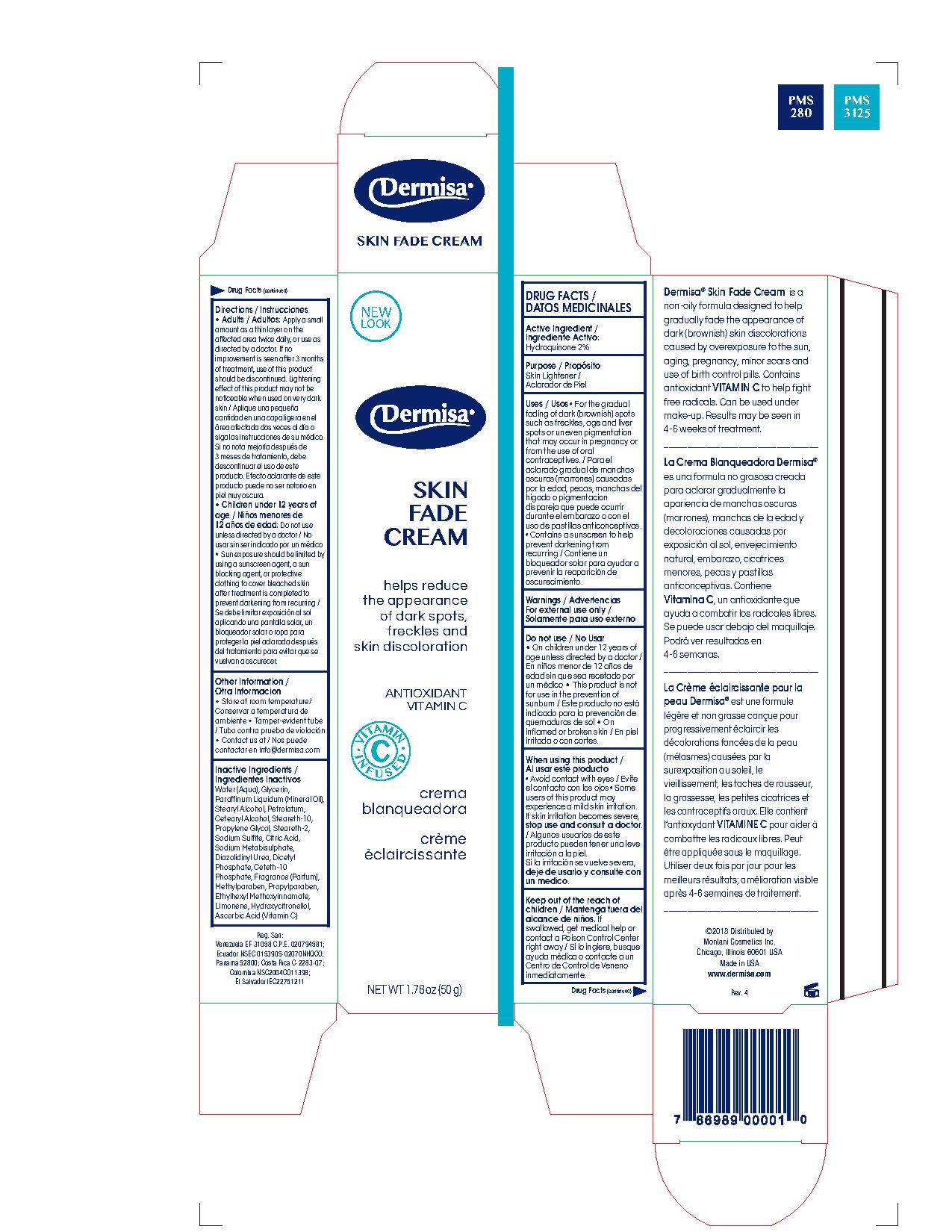 DRUG LABEL: Dermisa
NDC: 68343-005 | Form: CREAM
Manufacturer: Montani Cosmetics Inc
Category: otc | Type: HUMAN OTC DRUG LABEL
Date: 20180718

ACTIVE INGREDIENTS: HYDROQUINONE 2 g/100 g
INACTIVE INGREDIENTS: DIHEXADECYL PHOSPHATE; CITRIC ACID MONOHYDRATE; LIMONENE, (+)-; SODIUM SULFITE; DIAZOLIDINYL UREA; OCTINOXATE; HYDROXYCITRONELLOL; PROPYLENE GLYCOL; WATER; MINERAL OIL; GLYCERIN; STEARYL ALCOHOL; PETROLATUM; STEARETH-10; STEARETH-2; ASCORBIC ACID; SODIUM METABISULFITE; PROPYLPARABEN; METHYLPARABEN; CETOSTEARYL ALCOHOL; CETETH-10 PHOSPHATE

Drug Facts

Active Ingredient

Hydroquinone USP 2%
Octyl Dimethyl Paba 0.60%

Purpose

Skin Lightener

Uses

• For the gradual fading of dark (brownish) skin discolorations such as freckles, age and liver spots or uneven pigment that may occur due to sun overexposure, pregnancy or from the use of oral contraceptives.

Warnings

For external use only

Do not use

• On children under 12 years of age unless directed by a doctor • This product is not for use in the prevention of sunburn • On inflamed or broken skin

When using this product

• Avoid contact with the eyes • Some users of this product may experience a mild skin irritation, if skin irritation becomes severe stop use and consult a doctor

Keep out of reach of children

If swallowed, get medical help or contact a Poison Control Center right away

Directions

• Adults Apply a small amount as a thin layer to the affected areas twice daily or as directed by a doctor. If no improvement is seen after 3 months of treatment, use of this product should be discontinued.Lightening effect of this product may not be noticeable when used on very dark skin. • Children under 12 years of age Do not use unless directed by a doctor

• Sun exposure should be limited by using a sunscreen agent, or protective clothing to prevent bleached skin after treatment completed to prevent darkening from recurring

Other Information

• Store at room temperature • Tamper-evident tube • Contact us at contractar en info@dermisa.com

Inactive ingredients

Water (Aqua), Glycerin, Paraffinum Liquidum (Mineral Oil), Stearyl Alcohol, Petrolatum, Cetearyl Alcohol, Steareth-10, Propylene Glycol, Steareth-2, Sodium Sulfite, Citric Acid, Sodium Metabisulphate, Diazolidinyl Urea, Dicetyl Phosphate, Ceteth-10 Phosphate, Fragrance (Parfum), Methylparaben, Propylparaben, Ethylhexyl Methoxyinnamate, Limonene, Hydroxycitronellol, Ascorbic Acid (Vitamin C)